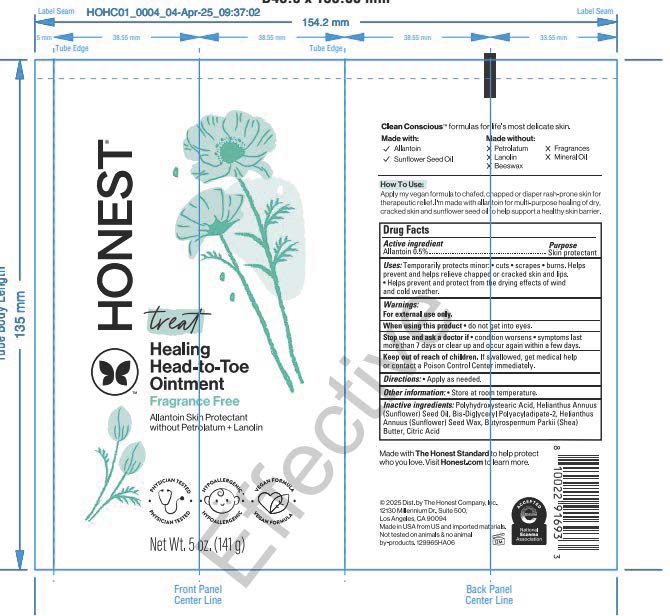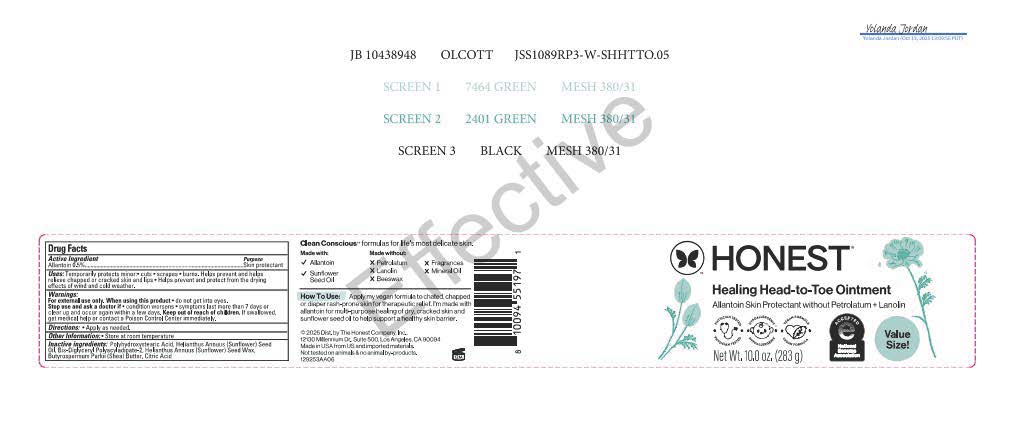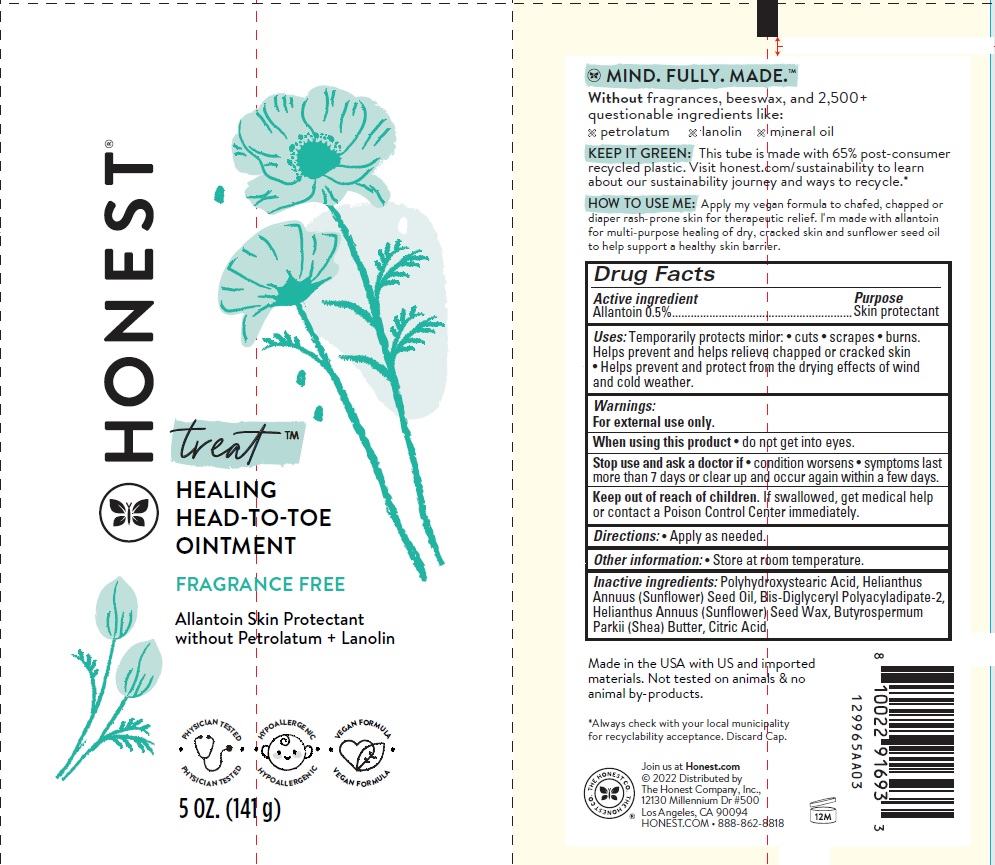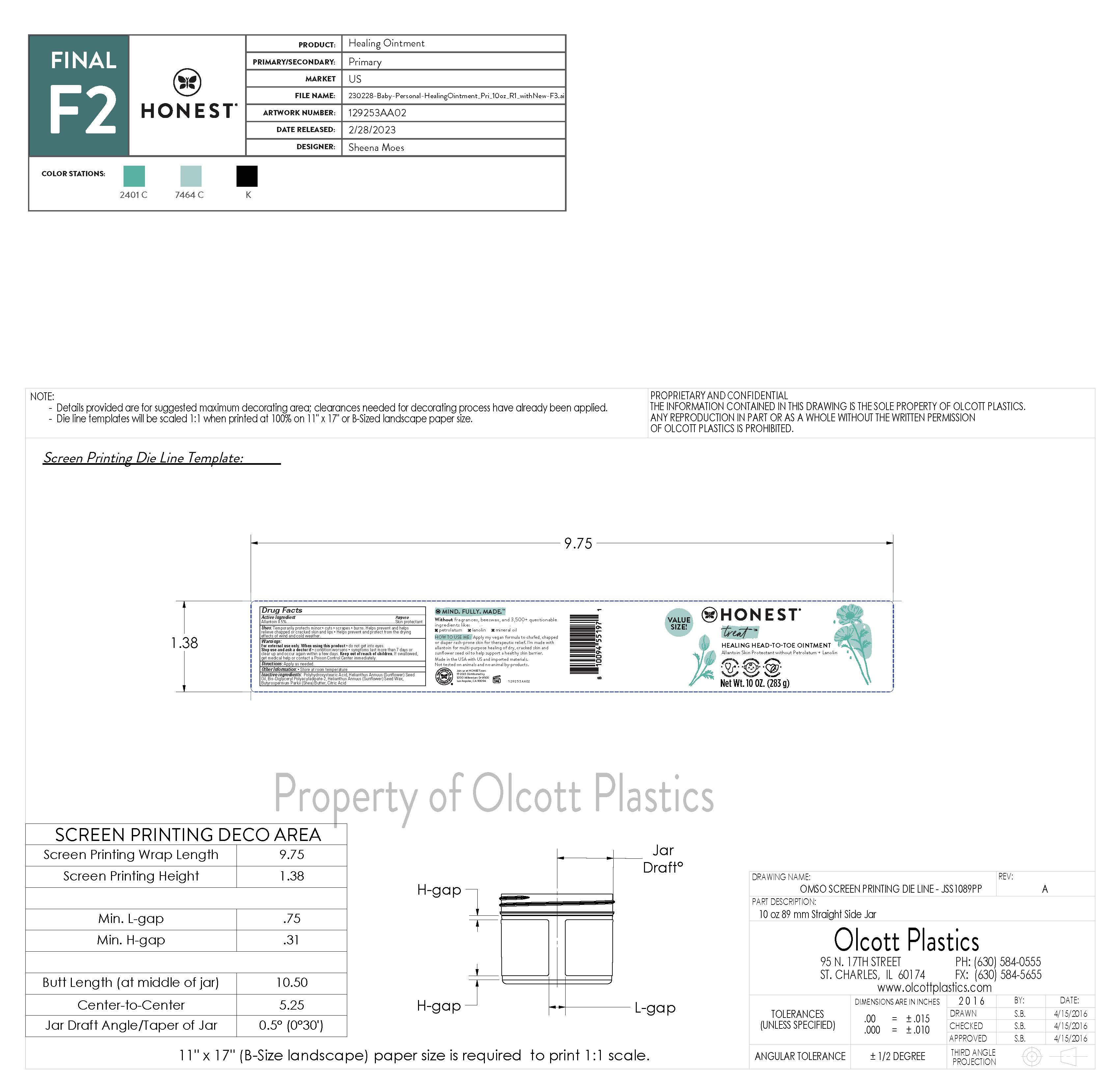 DRUG LABEL: Healing Head to Toe
NDC: 69366-508 | Form: OINTMENT
Manufacturer: The Honest Company, Inc
Category: otc | Type: HUMAN OTC DRUG LABEL
Date: 20251223

ACTIVE INGREDIENTS: ALLANTOIN 0.5 g/100 g
INACTIVE INGREDIENTS: SUNFLOWER OIL; BIS-DIGLYCERYL POLYACYLADIPATE-2; SHEA BUTTER; CITRIC ACID MONOHYDRATE; HELIANTHUS ANNUUS SEED WAX; POLYHYDROXYSTEARIC ACID (2300 MW)

Healing Head-to-Toe Ointment

Active ingredient Allantoin 0.5%

Purpose Skin protectant

INDICATIONS AND USAGE

Uses: Temporarily protects minor: • cuts • scrapes • burns.
Helps prevent and helps relieve chapped or cracked skin
• Helps prevent and protect from the drying effects of wind
and cold weather.

Warnings:

For external use only.

When using this product • do not get into eyes.

Stop use and ask a doctor if • condition worsens • symptoms last
more than 7 days or clear up and occur again within a few days.

Keep out of reach of children. If swallowed, get medical help
or contact a Poison Control Center immediately.

DOSAGE AND ADMINISTRATION

Directions: • Apply as needed.

Other information: • Store at room temperature.

Inactive ingredients: Polyhydroxystearic Acid, Helianthus

Annuus (Sunower) Seed Oil, Bis-Diglyceryl Polyacyladipate-2,

Helianthus Annuus (Sunower) Seed Wax, Butyrospermum

Parkii (Shea) Butter, Citric Acid

PACKAGE LABEL

HONEST® treat™

HEALING HEAD-TO-TOE OINTMENT

FRAGRANCE FREE

Allantoin Skin Protectant

without Petrolatum + Lanolin

5 oz (141 g)

Made in the USA with US and imported
materials. Not tested on animals & no
animal by-products.

Join us at Honest.com
© 2022 Distributed by
The Honest Company, Inc.,
12130 Millennium Dr #500
Los Angeles, CA 90094
HONEST.COM • 888-862-8818

PACKAGE LABEL

HONEST ® treat™

HEALING HEAD-TO-TOE OINTMENT

FRAGRANCE FREE

Allantoin Skin Protectant

without Petrolatum + Lanolin

10 oz (283 g)

Made in the USA with US and imported
materials. Not tested on animals & no
animal by-products.

Join us at Honest.com
© 2022 Distributed by
The Honest Company, Inc.,
12130 Millennium Dr #500
Los Angeles, CA 90094
HONEST.COM • 888-862-8818

PACKAGE LABEL

HONEST ® treat™

HEALING HEAD-TO-TOE OINTMENT

FRAGRANCE FREE

Allantoin Skin Protectant

without Petrolatum + Lanolin

5 oz (141 g)

Made in the USA with US and imported
materials. Not tested on animals & no
animal by-products.

Join us at Honest.com
© 2022 Distributed by
The Honest Company, Inc.,
12130 Millennium Dr #500
Los Angeles, CA 90094
HONEST.COM

PACKAGE LABEL

HONEST ® treat™

HEALING HEAD-TO-TOE OINTMENT

FRAGRANCE FREE

Allantoin Skin Protectant

without Petrolatum + Lanolin

10 oz (283 g)

Made in the USA with US and imported
materials. Not tested on animals & no
animal by-products.

Join us at Honest.com
© 2022 Distributed by
The Honest Company, Inc.,
12130 Millennium Dr #500
Los Angeles, CA 90094
HONEST.COM